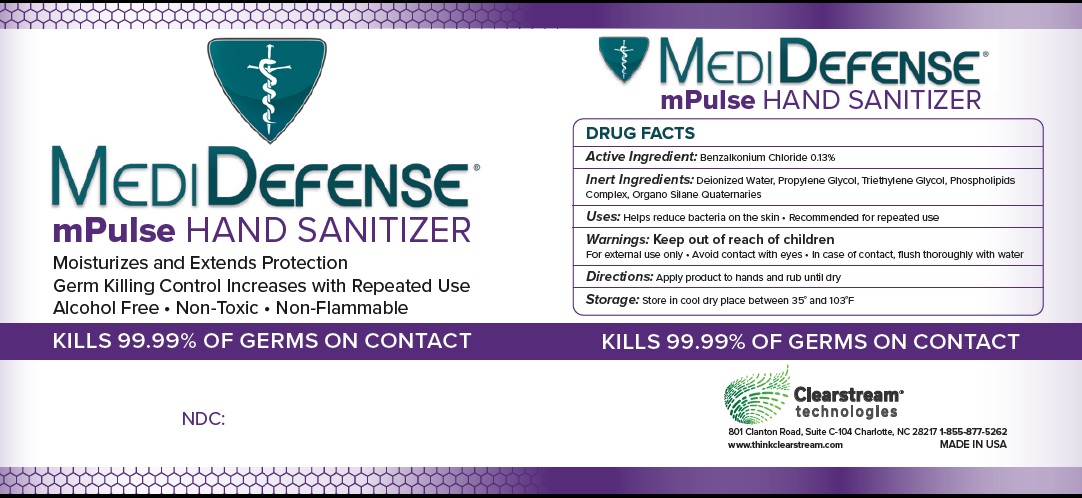 DRUG LABEL: mPulse Antimicrobial Hand Sanitizer
NDC: 78941-001 | Form: LIQUID
Manufacturer: ANTIMICROBIAL SOLUTIONS, LLC
Category: otc | Type: HUMAN OTC DRUG LABEL
Date: 20200616

ACTIVE INGREDIENTS: BENZALKONIUM CHLORIDE 0.13 g/0.1 L
INACTIVE INGREDIENTS: WATER; PROPYLENE GLYCOL; TRIETHYLENE GLYCOL

Active Ingredient

Benzalkonium Chloride 0.13%

Uses

- Helps reduce bacteria on the skin.
- Recommended for repeated use.

Warnings

- For external use only.
- Avoid contact with eyes.
- In case of contact, flush thoroughly with water.

Keep out of reach of children.

Directions

Apply product to hands and rub until dry.

Other information

Store in cool dry place between 35° and 103°F.

Inactive ingredients

Deionized Water, Propylene Glycol, Triethylene Glycol, Phospholipids Complex, Organo Silane Quaternaries.